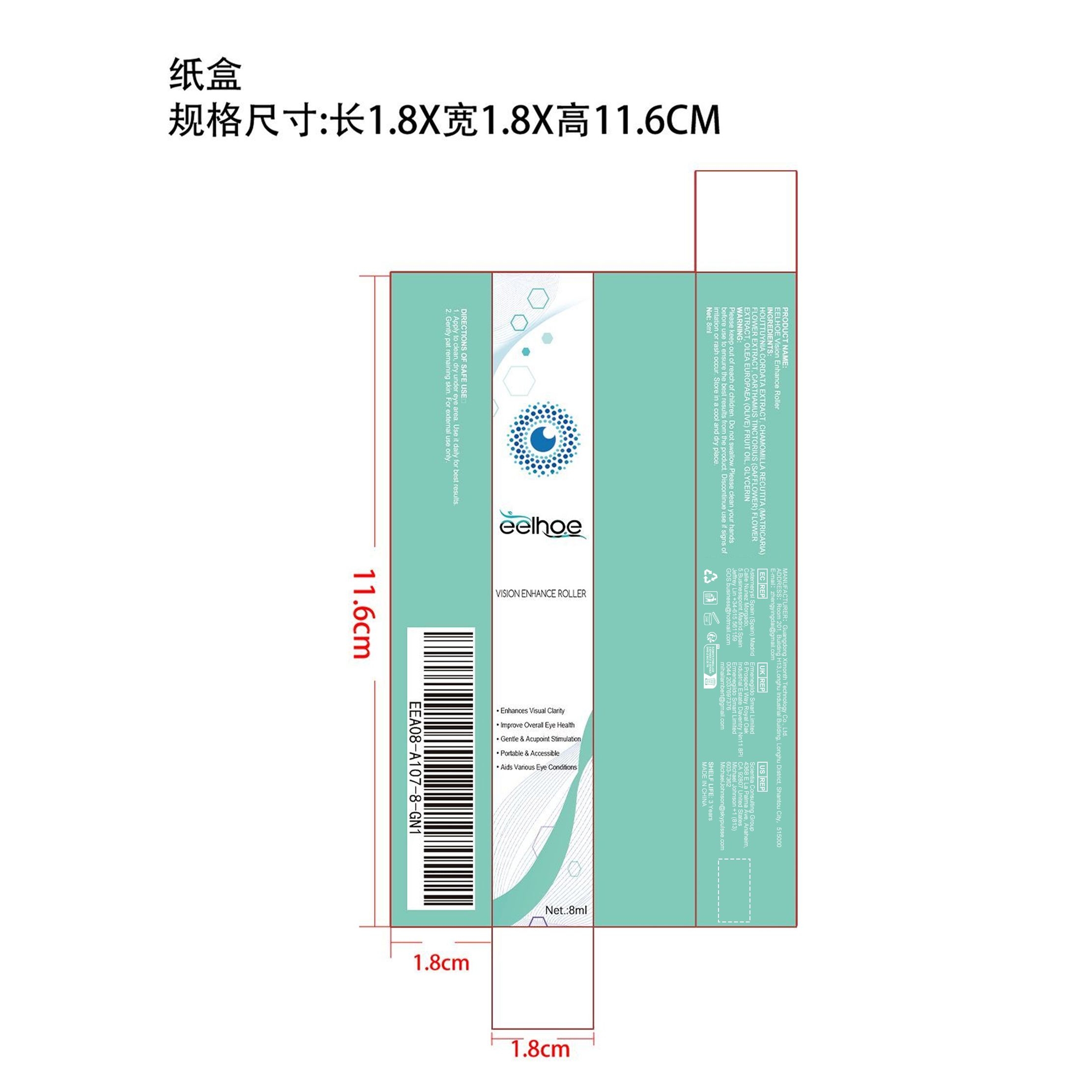 DRUG LABEL: EELHOE Vision Enhance Roller
NDC: 84660-032 | Form: LIQUID
Manufacturer: Guangdong Ximonth Technology Co., Ltd.
Category: otc | Type: HUMAN OTC DRUG LABEL
Date: 20240926

ACTIVE INGREDIENTS: CHAMOMILE 1.6 mg/8 mg; OLIVE OIL 0.8 mg/8 mg; HOUTTUYNIA CORDATA FLOWERING TOP 2 mg/8 mg; SAFFLOWER 1.2 mg/8 mg
INACTIVE INGREDIENTS: GLYCERIN 2.4 mg/8 mg

Active Ingredient(s)

HOUTTUYNIA CORDATA EXTRACT、CHAMOMILLA RECUTITA (MATRICARIA)FLOWER EXTRACT、
CARTHAMUS TINCTORIUS (SAFFLOWER) FLOWER EXTRACT、OLEA EUROPAEA (OLIVE) FRUIT OIL

Purpose

Enhances Visual Clarity

Use

1. Apply to clean, dry under eye area. Use it daily for best results.
2. Gently pat remaining skin. For external use only.

Warnings

Please keep out of reach of children.Do not swallow.Please clean your hands before use to ensure the best results from the product.Discontinue use if signs of irritation or rash occur.Store in a cool and dry place

Do not use

Discontinue use if signs of irritation or rash occur.

STOP USE

Discontinue use if signs of irritation or rash occur

KEEP OUT OF REACH OF CHILDREN

Please keep out of reach of children. Do not swallow.

STORAGE AND HANDLING

Avoid freezing and excessive heat above 40C (104F) ）
Store in a cool and dry place.

INACTIVE INGREDIENT

GLYCERIN